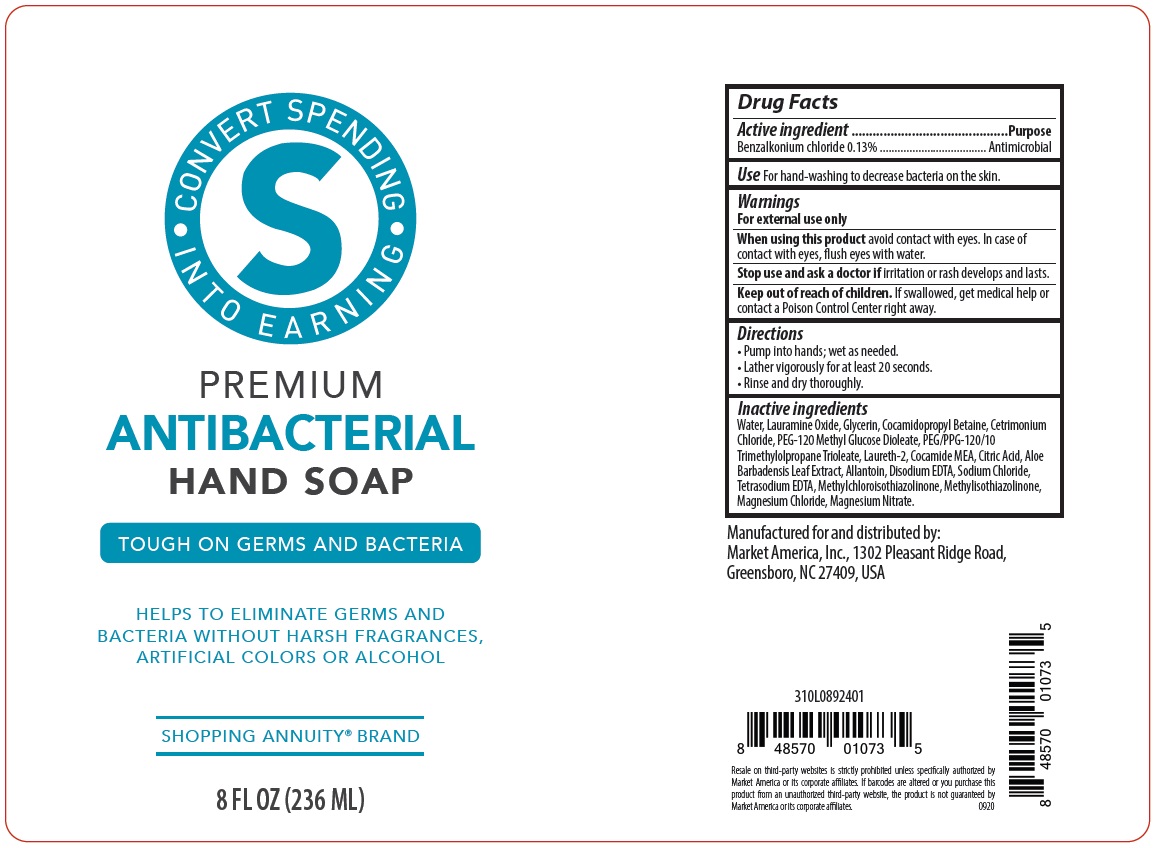 DRUG LABEL: Shopping Annuity Premium Anti-Bacterial HandSoap
NDC: 76209-118 | Form: LIQUID
Manufacturer: Market America, Inc.
Category: otc | Type: HUMAN OTC DRUG LABEL
Date: 20210312

ACTIVE INGREDIENTS: BENZALKONIUM CHLORIDE 0.13 g/100 mL
INACTIVE INGREDIENTS: WATER; LAURAMINE OXIDE; GLYCERIN; COCAMIDOPROPYL BETAINE; CETRIMONIUM CHLORIDE; PEG-120 METHYL GLUCOSE DIOLEATE; TRIMETHYLOLPROPANE TRIOLEATE; LAURETH-2; COCO MONOETHANOLAMIDE; CITRIC ACID MONOHYDRATE; ALOE VERA LEAF; ALLANTOIN; EDETATE DISODIUM ANHYDROUS; SODIUM CHLORIDE; EDETATE SODIUM; METHYLCHLOROISOTHIAZOLINONE; METHYLISOTHIAZOLINONE; MAGNESIUM CHLORIDE; MAGNESIUM NITRATE

SHOPPING ANNUITY® BRAND PREMIUM ANTIBACTERIAL HAND SOAP

Active ingredient

Benzalkonium chloride 0.13%

Purpose

Antimicrobial

Use

For hand-washing to decrease bacteria on the skin.

Warnings

For external use only

When using this product avoid contact with eyes. In case of contact with eyes, flush eyes with water.

Stop use and ask a doctor if irritation or rash develops and lasts.

Keep out of reach of children. If swallowed, get medical help or contact a Poison Control Center right away.

Directions

• Pump into hands; wet as needed.

• Lather vigorously for at least 20 seconds.

• Rinse and dry thoroughly.

Inactive ingredients

Water, Lauramine Oxide, Glycerin, Cocamidopropyl Betaine, Cetrimonium Chloride, PEG-120 Methyl Glucose Dioleate, PEG/PPG-120/10 Trimethylolpropane Trioleate, Laureth-2, Cocamide MEA, Citric Acid, Aloe Barbadensis Leaf Extract, Allantoin, Disodium EDTA, Sodium Chloride, Tetrasodium EDTA, Methylchloroisothiazolinone, Methylisothiazolinone, Magnesium Chloride, Magnesium Nitrate.

CONVERT SPENDING INTO EARNING

TOUGH ON GERMS AND BACTERIA

HELPS TO ELIMINATE GERMS AND BACTERIA WITHOUT HARSH FRAGRANCES, ARTIFICIAL COLORS OR ALCOHOL

Manufactured for and distributed by:
Market America, Inc., 1302 Pleasant Ridge Road,
Greensboro, NC 27409, USA

Resale on third-party websites is strictly prohibited unless specifically authorized by Market America or its corporate affiliates. If barcodes are altered or you purchase this product from an unauthorized third-party website, the product is not guaranteed by Market America or its corporate affiliates.